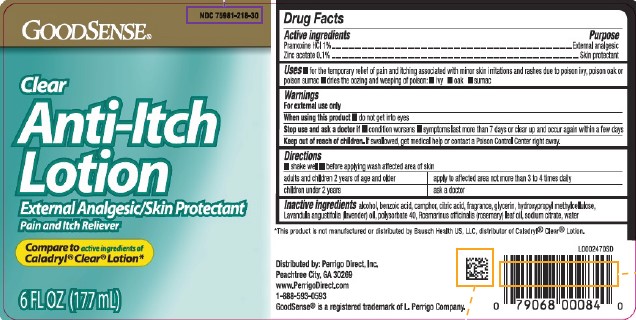 DRUG LABEL: Clear Anti-Itch
NDC: 75981-218 | Form: LOTION
Manufacturer: Perrigo Direct, Inc
Category: otc | Type: HUMAN OTC DRUG LABEL
Date: 20260219

ACTIVE INGREDIENTS: PRAMOXINE HYDROCHLORIDE 10 mg/1 mL; ZINC ACETATE 1 mg/1 mL
INACTIVE INGREDIENTS: ALCOHOL; BENZOIC ACID; CAMPHOR (SYNTHETIC); CITRIC ACID MONOHYDRATE; GLYCERIN; HYPROMELLOSE, UNSPECIFIED; LAVENDER OIL; POLYSORBATE 40; ROSEMARY OIL; SODIUM CITRATE; WATER

Good Sense 218.002/218AF
Clear Anti-Itch Lotion

Active ingredients

Pramoxine HCl 1%

Zinc acetate 0.1%

Purpose

External analgesic

Skin protectant

Uses

- for the temporary relief of pain and itching associated with minor skin irritations and rashes due to poison ivy, poison oak or poison sumac
- dries the oozing and weeping of poison: - ivy - oak - sumac

Warnings

For external use only

When using this product

- do not get into eyes

Stop use section and ask a doctor if

- condition worsens
- symptoms last more than 7 days or clear up and occur again within a few days

Keep out of reach of children.

If swallowed, get medical help or contact a Poison Control Center right away.

Directions

- shake well
- before applying wash affected area of skin

adults and children 2 years of age and older - apply to affected area not more than 3 to 4 times daily

children under 2 years - ask a doctor

Inactive ingredients

alcohol, benzoic acid, camphor, citric acid, fragrance, glycerin, hydroxypropyl methylcellulose, Lavandula angustifolia (lavender) oil, polysorbate 40, Rosmarinus officinalis (rosemary) leaf oil, sodium citrate, water

Disclaimer

*This product is not manufactured or distributed by Bausch Health US, LLC, distributor of Caladryl® Clear® Lotion.

Adverse reaction

Distributed by: Perrigo Direct, Inc.

Peachtree City, GA 30269

www.PerrigoDirect.com

1-888-593-0593

GoodSense®is a registered trademark of L. Perrigo Company.

Principal Display Panel

NDC 75981-218-30

GoodSENSE®

Clear Anti-Itch Lotion

External Analgesic/Skin Protectant

Pain and Itch Reliever

Compare to active ingredients of Caladryl® Clear® Lotion*

6 FL OZ (177 mL)